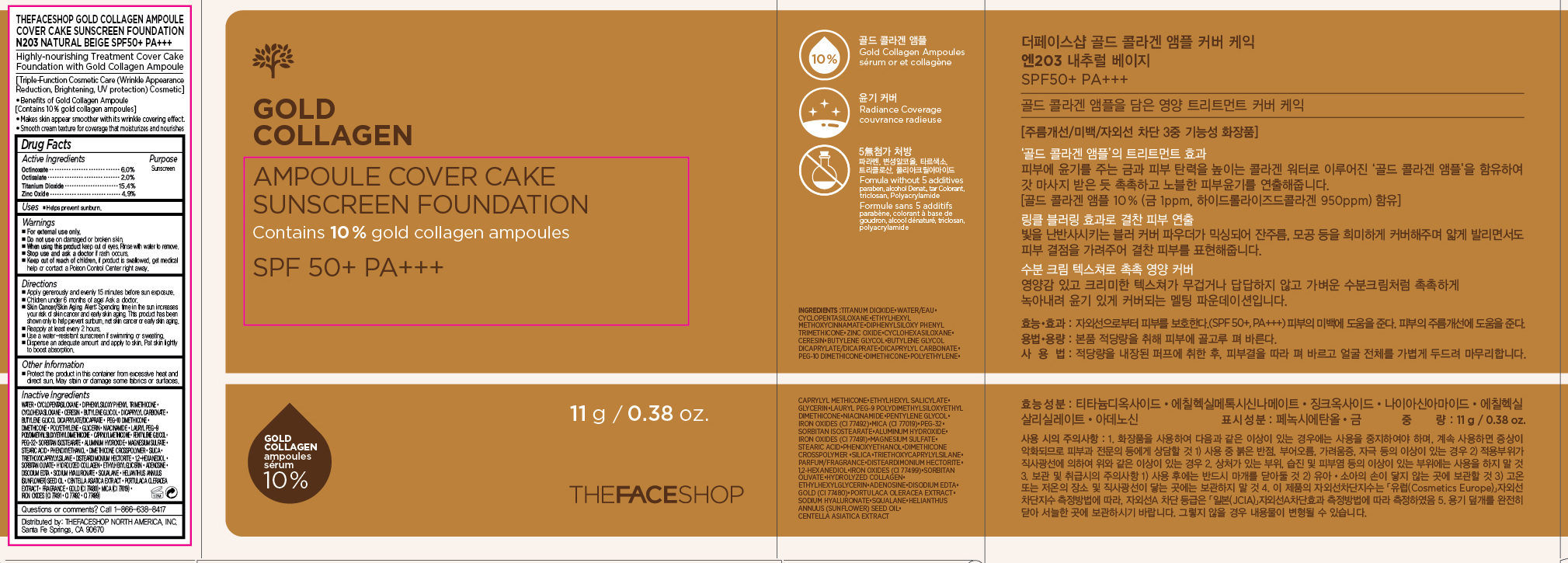 DRUG LABEL: GOLD COLLAGEN
NDC: 51523-260 | Form: POWDER
Manufacturer: THEFACESHOP CO., LTD.
Category: otc | Type: HUMAN OTC DRUG LABEL
Date: 20150810

ACTIVE INGREDIENTS: TITANIUM DIOXIDE 1.7 g/11 g; ZINC OXIDE 0.5 g/11 g; OCTINOXATE 0.7 g/11 g; OCTISALATE 0.2 g/11 g
INACTIVE INGREDIENTS: WATER

TFS GOLD COLLAGEN AMPOULE COVER CAKE SPF50 PA+++N203 34200260

Active Ingredients

Octinoxate 6.0 %
Octisalate 2.0 %
Titanium Dioxide 15.4 %
Zinc Oxide 4.9 %

Purpose

Sunscreen
Sunscreen
Sunscreen
Sunscreen

Uses

Helps prevent sunburn

Warnings

For external use only.

Do not use on damaged or broken skin

When using this product keep out of eyes. Rinse with water to remove.

Stop use and ask a doctor if rash occurs.

Keep out of reach of children. If product is swallowed, get medical help or contact a Poison Control Center right away.

Directions

Apply generously and evenly 15 minutes before sun exposure.
Children under 6 months of age: Ask a doctor.
Skin Cancer/Skin Aging Alert: Spending time in the sun increases your risk of skin cancer and early skin aging. This product has been shown only to help prevent sunburn, not skin cancer or early skin aging.
Reapply at least every 2 hours.
Use a water-resistant sunscreen if swimming or sweating.

Dispense an adequate amount onto the puff and apply to skin. Pat skin lightly to boost absorption.

Other Information

Protect the product in this container from excessive heat and direct sun.

May stain or damage some fabrics or surfaces.

Inactive Ingredients

Water, Cyclopentasiloxane, Diphenylsiloxy Phenyl Trimethicone, Cyclohexasiloxane, Ceresin, Butylene Glycol, Dicaprylyl Carbonate, Butylene Glycol Dicaprylate/Dicaprate, PEG-10 Dimethicone, Dimethicone, Polyethylene, Glycerin, Niacinamide, Lauryl PEG-9 Polydimethylsiloxyethyl Dimethicone, Caprylyl Methicone, Pentylene Glycol, PEG-32, Sorbitan Isostearate, Aluminum Hydroxide, Magnesium Sulfate, Stearic Acid, Phenoxyethanol, Dimethicone Crosspolymer, Silica, Triethoxycaprylylsilane, Disteardimonium Hectorite, 1,2-Hexanediol, Sorbitan Olivate, Hydrolyzed Collagen, Ethylhexylglycerin, Adenosine, Disodium EDTA, Sodium Hyaluronate, Squalane, Helianthus Annuus (Sunflower) Seed Oil, Centella Asiatica Extract, Portulaca Oleracea Extract, Fragrance, Gold (CI 77480), Mica (CI 77019), Iron Oxides (CI 77491, CI 77492, CI 77499)

Questions or comments? Call 1-866-638-8417

Distributed by:

THEFACESHOP NORTH AMERICA, INC.

Santa Fe Springs, CA 90670

PACKAGE LABEL

THEFACESHOP GOLD COLLAGEN
AMPOULE COVER CAKE SUNSCREEN FOUNDATION
N203 NATURAL BEIGE SPF50+ PA+++
Highly-nourishing Treatment Cover Cake Foundation
with Gold Collagen Ampoule
[Triple-Function Cosmetic Care (Wrinkle Appearance Reduction, Brightening, UV Protection) Cosmetic]
Benefits of Gold Collagen Ampoule
[Contains 10% gold collagen ampoules]
Makes skin appear smoother with its wrinkle covering effect
Smooth cream texture for coverage that moisturizes and nourishes